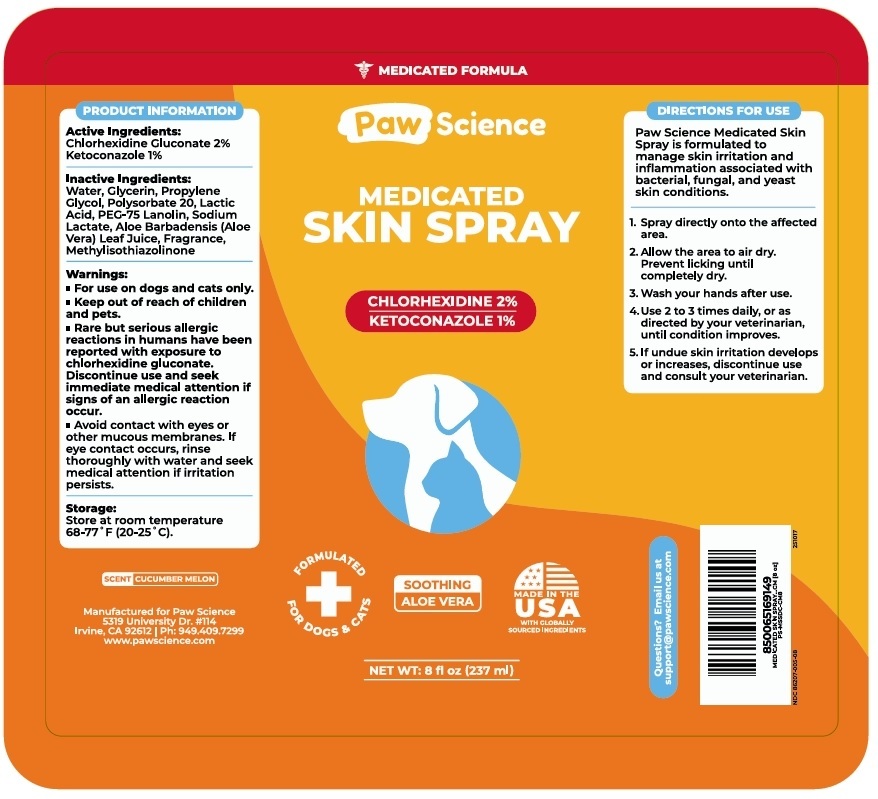 DRUG LABEL: Paw Science MEDICATED SKIN
NDC: 86207-005 | Form: SPRAY
Manufacturer: Pet Science LLC
Category: animal | Type: OTC ANIMAL DRUG LABEL
Date: 20251107

ACTIVE INGREDIENTS: CHLORHEXIDINE GLUCONATE 20 mg/1 mL; KETOCONAZOLE 10 mg/1 mL
INACTIVE INGREDIENTS: WATER; GLYCERIN; PROPYLENE GLYCOL; POLYSORBATE 20; LACTIC ACID, UNSPECIFIED FORM; PEG-75 LANOLIN; SODIUM LACTATE; ALOE VERA LEAF JUICE; METHYLISOTHIAZOLINONE

Paw Science MEDICATED SKIN SPRAY

Active Ingredients:

Chlorhexidine Gluconate 2%
Ketoconazole 1%

Inactive Ingredients:

Water, Glycerin, Propylene Glycol, Polysorbate 20, Lactic Acid, PEG-75 Lanolin, Sodium Lactate, Aloe Barbadensis (Aloe Vera) Leaf Juice, Fragrance, Methylisothiazolinone

Warnings:

• For use on dogs and cats only.

• Keep out of reach of children and pets.

• Rare but serious allergic reactions in humans have been reported with exposure to chlorhexidine gluconate. Discontinue use and seek immediate medical attention if signs of an allergic reaction occur.

• Avoid contact with eyes or other mucous membranes. If eye contact occurs, rinse thoroughly with water and seek medical attention if irritation persists.

Storage:

Store at room temperature 68-77˚F (20-25˚C).

DIRECTIONS FOR USE

Paw Science Medicated Skin Spray is formulated to manage skin irritation and inflammation associated with bacterial, fungal, and yeast skin conditions.

1. Spray directly onto the affected area.
2. Allow the area to air dry. Prevent licking until completely dry.
3. Wash your hands after use.
4. Use 2 to 3 times daily, or as directed by your veterinarian, until condition improves.
5. If undue skin irritation develops or increases, discontinue use and consult your veterinarian.

MEDICATED FORMULA

FORMULATED FOR DOGS & CATS

SOOTHING ALOE VERA

MADE IN THE USA WITH GLOBALLY SOURCED INGREDIENTS

Questions? Email us at support@pawscience.com

SCENT CUCUMBER MELON

Manufactured for Paw Science
5319 University Dr. #114
Irvine, CA 92612 | Ph: 949.409.7299
www.pawscience.com